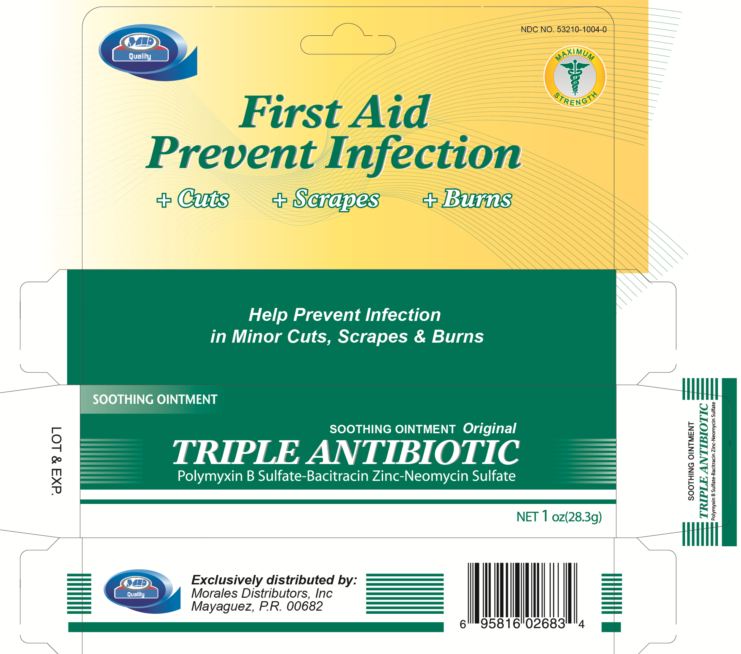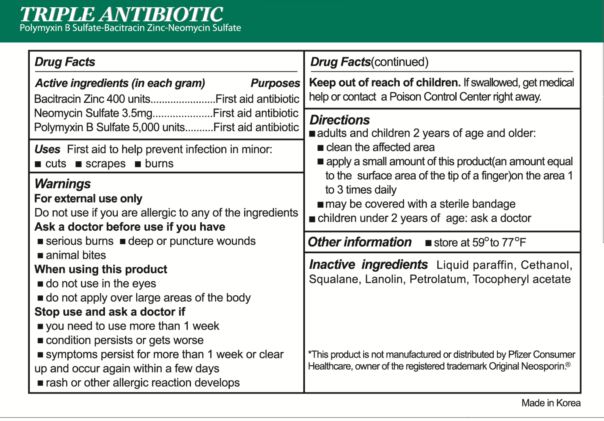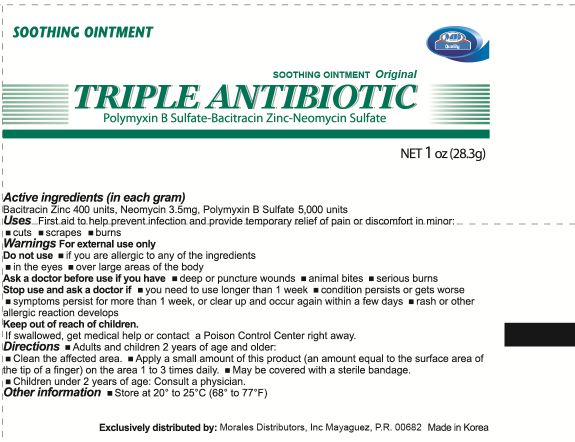 DRUG LABEL: Triple Antibiotic
                
                
NDC: 53210-1004 | Form: OINTMENT
Manufacturer: Morales Distributors Inc.
Category: otc | Type: HUMAN OTC DRUG LABEL
Date: 20121001

ACTIVE INGREDIENTS: BACITRACIN ZINC 400 U/1 g; NEOMYCIN SULFATE 3.5 mg/1 g; POLYMYXIN B SULFATE 5000 U/1 g
INACTIVE INGREDIENTS: MINERAL OIL; SQUALANE; LANOLIN; PETROLATUM; .ALPHA.-TOCOPHEROL ACETATE

Triple Antibiotic

Active ingredients (in each gram)

Bacitracin Zinc 400 units

Neomycin Sulfate 3.5mg

Polymyxin B Sulfate 5,000 units

Purposes

First aid antibiotic

Uses

First aid to help prevent infection in minor:

- cuts
- scrapes
- burns

Warnings

For external use only

Do not use if you are allergic to any of the ingredients

Ask a doctor before use if you have

- serious burns
- deep or puncture wounds
- animal bites

When using this product

- do not use in the eyes
- do not apply over large areas of the body

Stop use and ask a doctor if

- you need to use more than 1 week
- condition persists or gets worse
- symptoms persist for more than 1 week or clear up and occur again within a few days
- rash or other allergic reaction develops

Keep out of reach of children.

If swallowed, get medical help or contact a Poison Control Center right away.

Directions

- adults and children 2 years of age and older:
-
  - clean the affected area
  - apply a small amount of this product(an amount equal to the surface area of the tip of a finger)on the area 1 to 3 times daily
  - may be covered with a sterile bandage
- children under 2 years of age: ask a doctor

Other information

store at 59 degrees to 77 degrees Fahrenheit

Inactive ingredients

Liquid paraffin, Cethanol, Squalane, Lanolin, Petrolatum, Tocopheryl acetate

Package label

NDC NO. 53210-1004-0

First Aid Prevent Infection

Cuts Scrapes Burns

Maximum Strength

Help Prevent Infection in Minor Cuts, Scrapes and Burns

Soothing Ointment

Original
TRIPLE ANTIBIOTIC
Polymyxin B Sulfate-Bacitracin Zinc-Neomycin Sulfate

Net 1 oz(28.3g)

Exclusively distributed by:
Morales Distributors, Inc
Mayaguez, P.R. 00682

This product is not manufactured or distributed by Pfizer Consumer Healthcare, owner of the registered trademark Original Neosporin (R)

Made in Korea